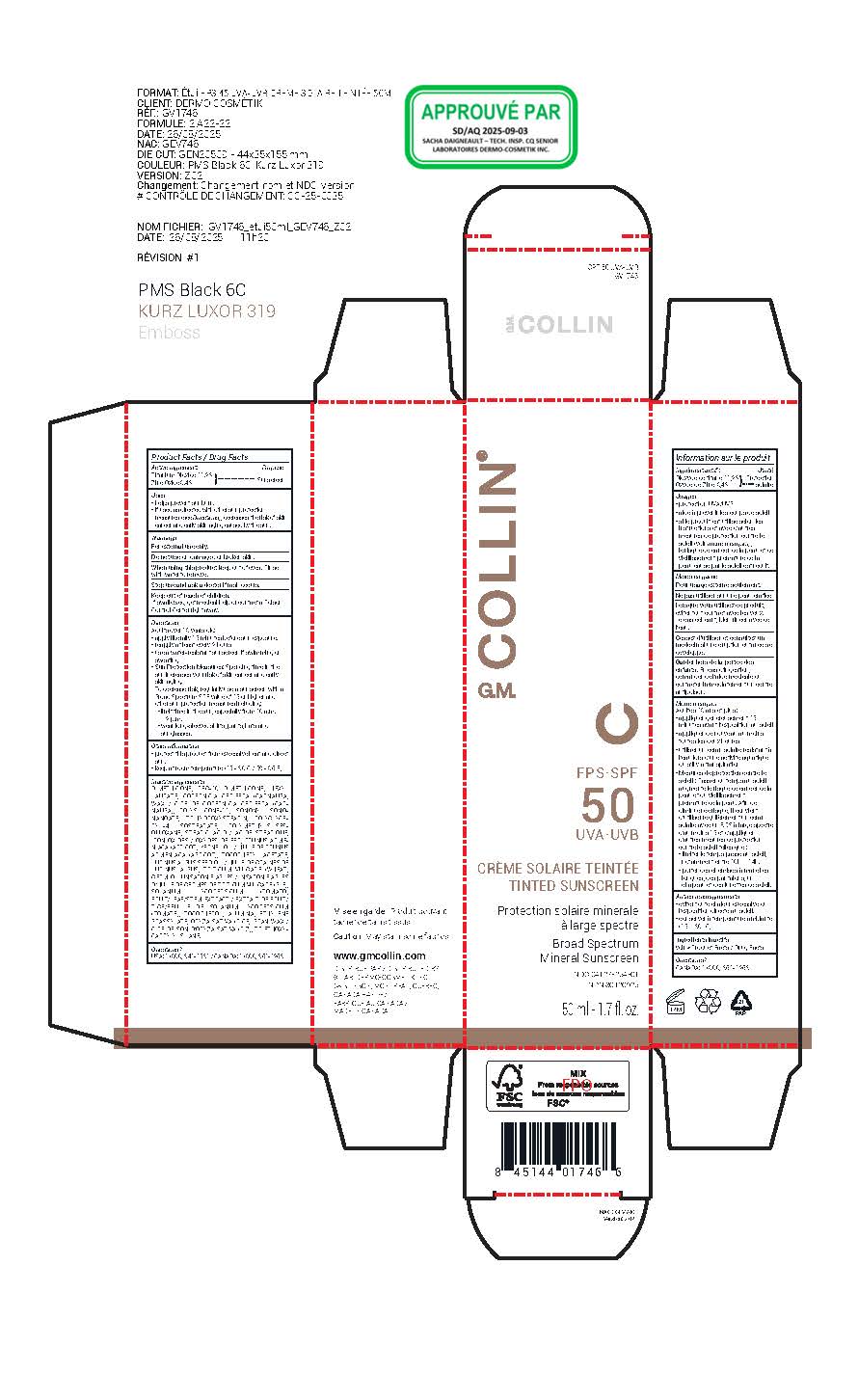 DRUG LABEL: G.M. Collin FPS-SPF 50 UVA-UVB TINTED SUNSCREEN
NDC: 64127-254 | Form: CREAM
Manufacturer: LABORATOIRES DERMO-COSMETIK INC.
Category: otc | Type: HUMAN OTC DRUG LABEL
Date: 20251222

ACTIVE INGREDIENTS: ZINC OXIDE 8.4 g/100 g; TITANIUM DIOXIDE 11.2 g/100 g
INACTIVE INGREDIENTS: APRICOT KERNEL OIL; DIMETHICONE/VINYL DIMETHICONE CROSSPOLYMER (SOFT PARTICLE); TRIHYDROXYSTEARIN; ALUMINA; FERROSOFERRIC OXIDE; STEARIC ACID; HEXYL LAURATE; FERRIC OXIDE RED; ETHYLENE BRASSYLATE; ORYZA SATIVA (RICE) BRAN; SOLANUM LYCOPERSICUM FRUITING TOP; LUPINUS ALBUS SEED OIL; ALPHA-TOCOPHEROL ACETATE; COPERNICIA CERIFERA (CARNAUBA) WAX; FERRIC OXIDE YELLOW; TRITICUM VULGARE (WHEAT) GERM OIL UNSAPONIFIABLES; TRIETHOXYCAPRYLYLSILANE; TOCOPHEROL; PEG-10 DIMETHICONE (220 CST); POLYGLYCERYL-4 ISOSTEARATE; POLYMETHYLSILSESQUIOXANE (4.5 MICRONS); ISONONYL ISONONANOATE; DIMETHICONE

SPF 50 UVA-UVB TINTED SUNSCREEN

Product Facts / Drug Facts

Active ingredients

Titanium Dioxide 11.2%

Zinc Oxide 8.4%

Purpose

Sunscreen

Uses

• helps prevent sunburn.
• if used as directed with other sun protection
measures (see Directions), decreases the risk of skin
cancer and early skin aging caused by the sun.

Warnings

For external use only.

Do not use on damaged or broken skin.

When using this product keep out of eyes. Rinse
with water to remove.

Stop use and ask a doctor if rash occurs.

Keep out of reach of children.
If swallowed, get medical help or contact a Poison
Control Center right away.

Directions

Adults over 18 years old:
• apply liberally 15 minutes before sun exposure.
• reapply at least every 2 hours
• use a water-resistant sunscreen if swimming or sweating
• Sun Protection Measures: Spending time in the sun increases your risk of skin cancer and early skin aging.
To decrease risk, regularly use a sunscreen with a Broad Spectrum SPF value of 15 or higher and other sun protection measures including:
• limit time in the sun, especially from 10 a.m. – 2 p.m.
• wear long-sleeved shirts, pants, hats and sunglasses.

Other informations

• protect this product from excessive heat and direct sun.
• keep at room temperature (15 - 30˚C / 59 - 86˚F)

Inactive ingredients

LAURATE, COPERNICIA CERIFERA (CARNAUBA) WAX / CIRE DE COPERNICIA CERIFERA (CARNAUBA), POLYSILICONE-11, ISONONYL ISONONANOATE, TRIHYDROXYSTEARIN, POLYGLYCERYL- 4 ISOSTEARATE, POLYMETHYLSILSESQUIOXANE, STEARIC ACID / ACIDE STÉARIQUE, IRON OXIDES / OXYDES DE FER, PRUNUS ARMENIACA (APRICOT) KERNEL OIL / HUILE DE PRUNUS ARMENIACA (ABRICOT), TOCOPHERYL ACETATE, LUPINUS ALBUS SEED OIL / HUILE DE GRAINES DE LUPINUS ALBUS, TRITICUM VULGARE (WHEAT) GERM OIL UNSAPONIFIABLES / INSAPONIFIABLES D’HUILE DE GERMES DE TRITICUM VULGARE (BLÉ), SOLANUM LYCOPERSICUM (TOMATO) FRUIT/LEAF/STEM EXTRACT / EXTRAIT DE FRUIT/ TIGE/FEUILLE DE SOLANUM LYCOPERSICUM (TOMATE), TOCOPHEROL, ALUMINA, ETHYLENE BRASSYLATE, ORYZA SATIVA (RICE) BRAN WAX / CIRE DE SON D’ORYZA SATIVA (RIZ), TRIETHOXYCAPRYLYLSILANE.

Questions?

USA: 1 (800) 341-1531 / CANADA: 1 (800) 361-1263

www.gmcollin.com
DISTRIBUÉ PAR / DISTRIBUTED BY:
® LAB. DERMO-COSMETIK INC.
68 STINSON, MONTREAL, QUEBEC,
CANADA H4N 2E7
FABRIQUÉ AU CANADA /
MADE IN CANADA